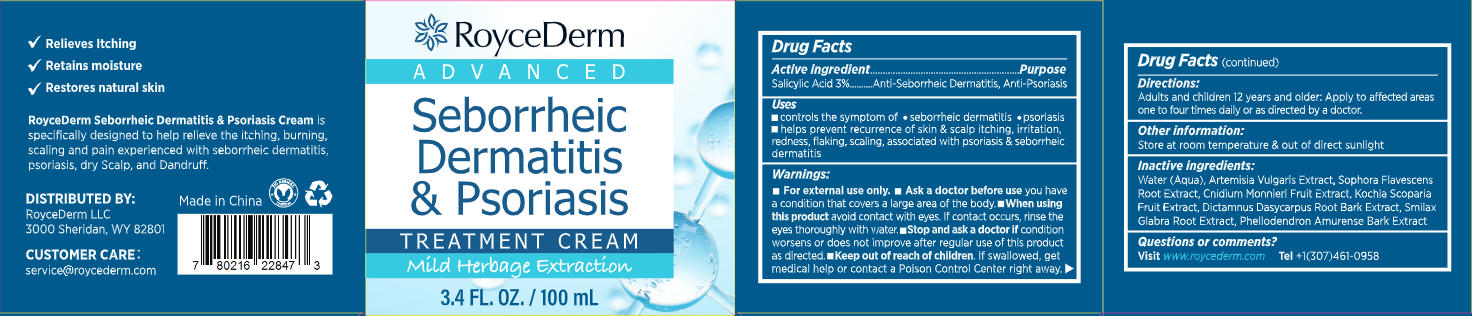 DRUG LABEL: RoyceDerm Seborrheic Dermatitis and Psoriasis Treatment cream
NDC: 85424-014 | Form: CREAM
Manufacturer: RoyceDerm LLC
Category: otc | Type: HUMAN OTC DRUG LABEL
Date: 20260128

ACTIVE INGREDIENTS: SALICYLIC ACID 3 g/100 g
INACTIVE INGREDIENTS: WATER; BASSIA SCOPARIA FRUIT; DICTAMNUS DASYCARPUS ROOT BARK; SMILAX GLABRA WHOLE; SOPHORA FLAVESCENS ROOT; CNIDIUM MONNIERI FRUIT OIL; PHELLODENDRON AMURENSE BARK; ARTEMISIA VULGARIS OIL

Initial Drug Listing - RoyceDerm Seborrheic Dermatitis & Psoriasis Treatment Cream- 85424-014-01

ACTIVE INGREDIENT

Salicylic Acid 3%

PURPOSE

Anti-Seborrheic Dermatitis, Anti-Psoriasis

DOSAGE AND ADMINISTRATION

- Controls the symptom of seborrheic dermatitis & psoriasis
- Helps prevent recurrence of skin & scalp itching, irritation, redness, flaking, scaling, associated with psoriasis & seborrheic dematitis

WARNINGS

For external use only.

- Ask a doctor before use you havea condition that covers a large area of the body.
- When usingthis product avoid contact with eyes. If contact occurs, rinse theeyes thoroughly with water.
- Stop and ask a doctor if conditionworsens or does not improve after regular use of this productas directed.

KEEP OUT OF REACH OF CHILDREN

If swallowed, getmedical help or contact a Poison Control Center right away.

INDICATIONS AND USAGE

Adults and children 12 years and older: Apply to affected areasone to four times daily or as directed by a doctor.

OTHER SAFETY INFORMATION

Store at room temperature & out of direct sunlight

INACTIVE INGREDIENT

Water (Aqua), Artemisia Vulgaris Extract, Sophora Flavescens Root Extract, Cnidium Monnieri Fruit Extract, Kochia ScopariaFruit Extract, Dictamnus Dasycarpus Root Bark Extract, Smilax Glabra Root Extract, Phellodendron Amurense Bark Extract

QUESTIONS

Visit www.roycederm.com
Tel+1(307)461-0958